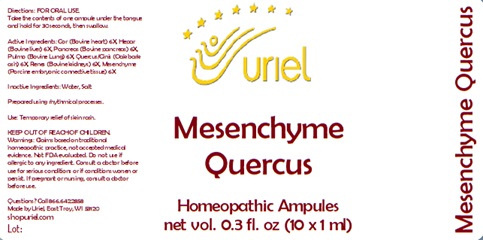 DRUG LABEL: Mesenchyme Quercus
NDC: 48951-7205 | Form: LIQUID
Manufacturer: Uriel Pharmacy Inc.
Category: homeopathic | Type: HUMAN OTC DRUG LABEL
Date: 20241205

ACTIVE INGREDIENTS: BEEF HEART 6 [hp_X]/1 mL; MAMMAL LIVER 6 [hp_X]/1 mL; SUS SCROFA PANCREAS 6 [hp_X]/1 mL; SUS SCROFA LUNG 6 [hp_X]/1 mL; QUERCUS ROBUR WHOLE 6 [hp_X]/1 mL; PORK KIDNEY 6 [hp_X]/1 mL; BOS TAURUS CARTILAGE 6 [hp_X]/1 mL
INACTIVE INGREDIENTS: WATER; SODIUM CHLORIDE

Mesenchyme Quercus

INDICATIONS AND USAGE

Directions: FOR ORAL USE.

DOSAGE AND ADMINISTRATION

Take the contents of one ampule under the tongue and hold for 30 seconds, then swallow.

ACTIVE INGREDIENT

Active Ingredients: Cor (Bovine heart) 6X, Hepar (Bovine liver) 6X, Pancreas (Bovine pancreas) 6X, Pulmo (Bovine Lung) 6X, Quercus/Cinis (Oak bark ash) 6X, Renes (Bovine kidneys) 6X, Mesenchyme (Porcine embryonic connective tissue) 6X

Inactive Ingredients: Water, Salt

Prepared using rhythmical processes.

PURPOSE

Use: Temporary relief of skin rash.

KEEP OUT OF REACH OF CHILDREN.

WARNINGS

Warnings: Claims based on traditional homeopathic practice, not accepted medical evidence. Not FDA evaluated. Do not use if allergic to any ingredient. Consult a doctor before use for serious conditions or if conditions worsen or persist. If pregnant or nursing, consult a doctor before use.

QUESTIONS

Questions? Call 866.642.2858 Made by Uriel, East Troy, WI 53120 shopuriel.com Lot: